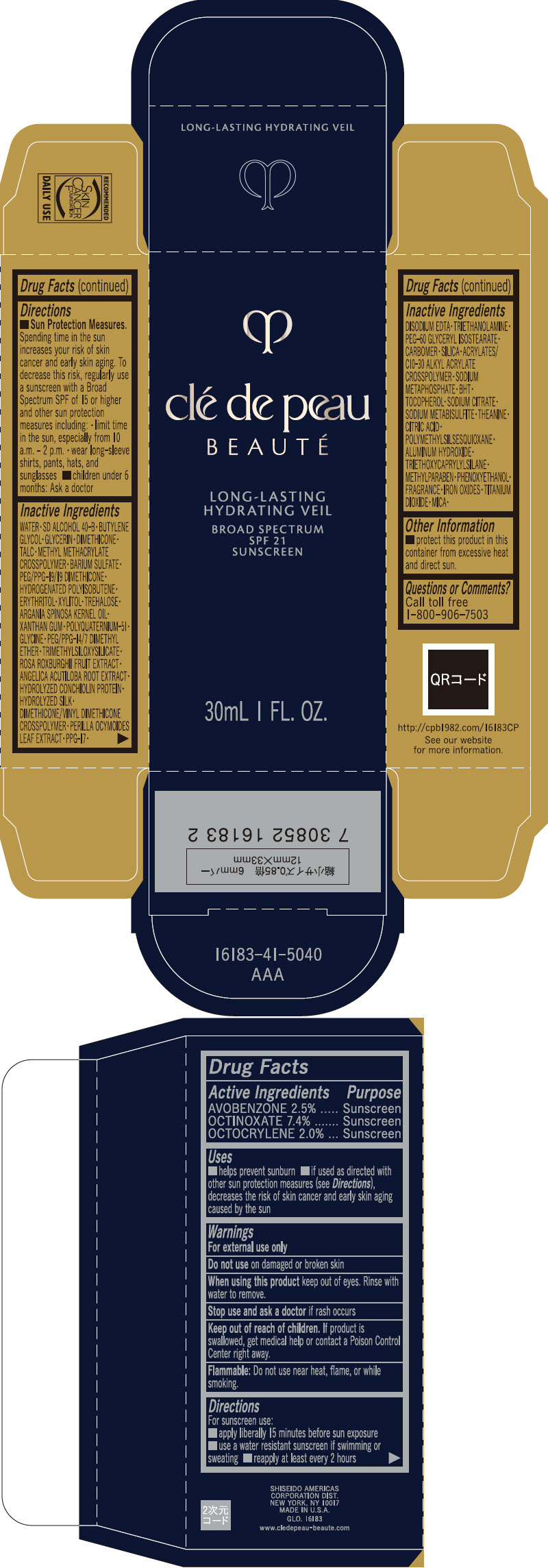 DRUG LABEL: cle de peau BEAUTE LONG-LASTING HYDRATING VEIL
NDC: 58411-623 | Form: EMULSION
Manufacturer: SHISEIDO AMERICAS CORPORATION
Category: otc | Type: HUMAN OTC DRUG LABEL
Date: 20260105

ACTIVE INGREDIENTS: AVOBENZONE 0.795 g/30 mL; OCTINOXATE 2.38 g/30 mL; OCTOCRYLENE 0.635 g/30 mL
INACTIVE INGREDIENTS: WATER; BUTYLENE GLYCOL; GLYCERIN; DIMETHICONE; TALC; METHYL METHACRYLATE/GLYCOL DIMETHACRYLATE CROSSPOLYMER; BARIUM SULFATE; PEG/PPG-19/19 DIMETHICONE; HYDROGENATED POLYISOBUTENE (1300 MW); XYLITOL; ERYTHRITOL; PPG-17; EDETATE DISODIUM; TROLAMINE; PEG-60 GLYCERYL ISOSTEARATE; METHYLPARABEN; CARBOMER HOMOPOLYMER, UNSPECIFIED TYPE; TREHALOSE; ARGAN OIL; SILICON DIOXIDE; CARBOMER INTERPOLYMER TYPE A (ALLYL SUCROSE CROSSLINKED); SODIUM POLYMETAPHOSPHATE; BUTYLATED HYDROXYTOLUENE; XANTHAN GUM; .ALPHA.-TOCOPHEROL; SODIUM CITRATE, UNSPECIFIED FORM; SODIUM METABISULFITE; POLYQUATERNIUM-51 (2-METHACRYLOYLOXYETHYL PHOSPHORYLCHOLINE/N-BUTYL METHACRYLATE; 3:7); FERRIC OXIDE RED; FERRIC OXIDE YELLOW; FERROSOFERRIC OXIDE; GLYCINE; THEANINE; PEG/PPG-14/7 DIMETHYL ETHER; PHENOXYETHANOL; TITANIUM DIOXIDE; CITRIC ACID MONOHYDRATE; TRIMETHYLSILOXYSILICATE (M/Q 0.6-0.8); ROSA ROXBURGHII FRUIT; MICA; ANGELICA ACUTILOBA ROOT; POLYMETHYLSILSESQUIOXANE (4.5 MICRONS); DIMETHICONE/VINYL DIMETHICONE CROSSPOLYMER (SOFT PARTICLE); PERILLA FRUTESCENS LEAF; ALUMINUM HYDROXIDE; TRIETHOXYCAPRYLYLSILANE

clé de peau BEAUTÉ LONG-LASTING HYDRATING VEIL

Drug Facts

ACTIVE INGREDIENT

Active ingredients | Purpose
AVOBENZONE 2.5% | Sunscreen
OCTINOXATE 7.4% | Sunscreen
OCTOCRYLENE 2.0% | Sunscreen

Uses

- helps prevent sunburn
- if used as directed with other sun protection measures (see Directions), decreases the risk of skin cancer and early skin aging caused by the sun

Warnings

For external use only

Do not use on damaged or broken skin

WHEN USING

When using this productkeep out of eyes. Rinse with water to remove.

Stop use and ask a doctorif rash occurs.

Keep out of reach of children.If product is swallowed, get medical help or contact a Poison Control Center right away.

Flammable:Do not use near heat, flame, or while smoking.

Directions

For sunscreen use:

- apply liberally 15 minutes before sun exposure
- use a water resistant sunscreen if swimming or sweating
- reapply at least every two hours
- Sun Protection Measures. Spending time in the sun increases your risk of skin cancer and early skin aging. To decrease this risk, regularly use a sunscreen with a broad spectrum SPF of 15 or higher and other sun protection measures including:
  - limit time in the sun, especially from 10 a.m. – 2 p.m.
  - wear long-sleeve shirts, pants, hats, and sunglasses
  - children under 6 months: Ask a doctor

Inactive Ingredients

WATER▪SD ALCOHOL 40-B▪BUTYLENE GLYCOL▪GLYCERIN▪DIMETHICONE▪TALC▪METHYL METHACRYLATE CROSSPOLYMER▪BARIUM SULFATE▪PEG/PPG-19/19 DIMETHICONE▪HYDROGENATED POLYISOBUTENE▪ERYTHRITOL▪XYLITOL▪TREHALOSE▪ARGANIA SPINOSA KERNEL OIL▪XANTHAN GUM▪POLYQUATERNIUM-51▪GLYCINE▪PEG/PPG-14/7 DIMETHYL ETHER▪TRIMETHYLSILOXYSILICATE▪ROSA ROXBURGHII FRUIT EXTRACT▪ANGELICA ACUTILOBA ROOT EXTRACT▪HYDROLYZED CONCHIOLIN PROTEIN▪HYDROLYZED SILK▪DIMETHICONE/VINYL DIMETHICONE CROSSPOLYMER▪PERILLA OCYMOIDES LEAF EXTRACT▪PPG-17▪DISODIUM EDTA▪TRIETHANOLAMINE▪PEG-60 GLYCERYL ISOSTEARATE▪CARBOMER▪SILICA▪ACRYLATES/C10-30 ALKYL ACRYLATE CROSSPOLYMER▪SODIUM METAPHOSPHATE▪BHT▪TOCOPHEROL▪SODIUM CITRATE▪SODIUM METABISULFITE▪THEANINE▪CITRIC ACID▪POLYMETHYLSILSESQUIOXANE▪ALUMINUM HYDROXIDE▪TRIETHOXYCAPRYLYLSILANE▪METHYLPARABEN▪PHENOXYETHANOL▪FRAGRANCE▪IRON OXIDES▪TITANIUM DIOXIDE▪MICA▪

Other information

Protect this product in this container from excessive heat and direct sun.

Questions or comments?

Call toll free 1-800-906-7503

PRINCIPAL DISPLAY PANEL - 30 mL Tube Carton

clé de peau

BEAUTÉ

LONG-LASTING
HYDRATING VEIL

BROAD SPECTRUM
SPF 21
SUNSCREEN

30mL 1 FL. OZ.